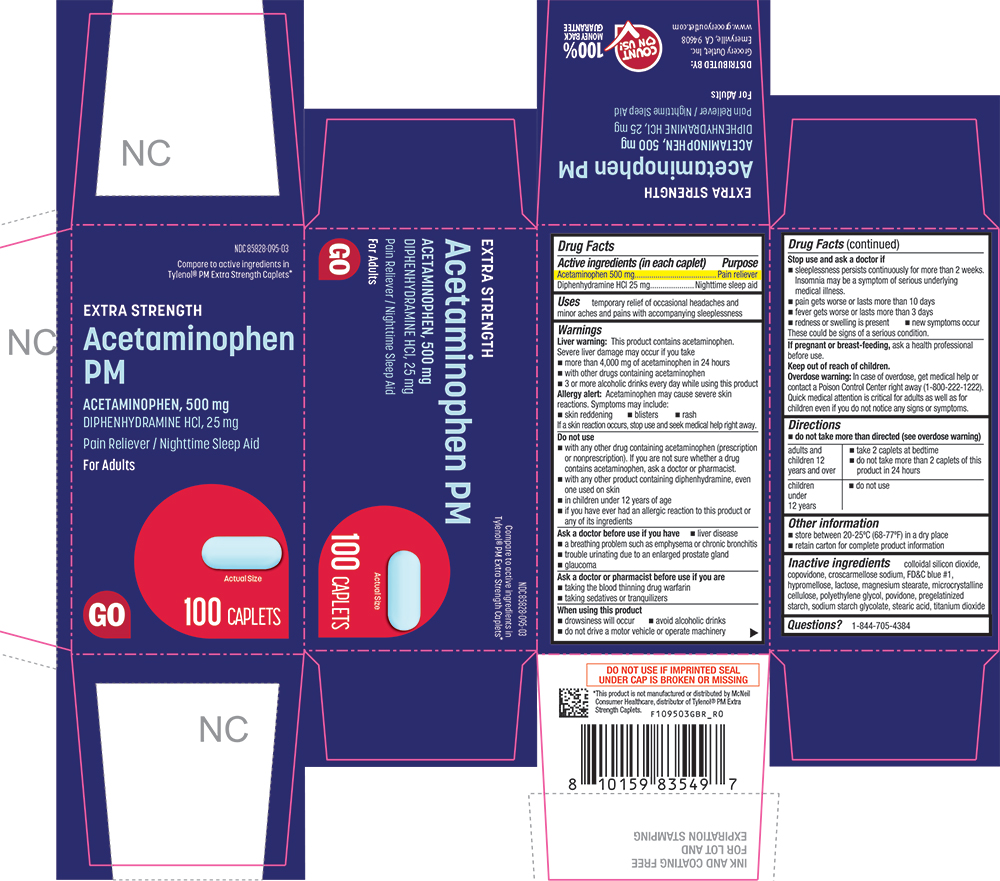 DRUG LABEL: Acetaminophen PM
NDC: 85828-095 | Form: TABLET, COATED
Manufacturer: Grocery Outlet, Inc.
Category: otc | Type: HUMAN OTC DRUG LABEL
Date: 20260218

ACTIVE INGREDIENTS: ACETAMINOPHEN 500 mg/1 1; DIPHENHYDRAMINE HYDROCHLORIDE 25 mg/1 1
INACTIVE INGREDIENTS: SODIUM STARCH GLYCOLATE TYPE A CORN; STEARIC ACID; TITANIUM DIOXIDE; SILICON DIOXIDE; COPOVIDONE K25-31; CROSCARMELLOSE SODIUM; FD&C BLUE NO. 1; HYPROMELLOSES; LACTOSE; MAGNESIUM STEARATE; CELLULOSE, MICROCRYSTALLINE; POLYETHYLENE GLYCOL, UNSPECIFIED; POVIDONE, UNSPECIFIED; STARCH, PREGELATINIZED CORN

1095-GBR-2026-0218

Drug Facts

ACTIVE INGREDIENT

Active ingredients (in each caplet) | Purpose
Acetaminophen 500 mg | Pain reliever
Diphenhydramine HCl 25 mg | Nighttime sleep aid

Uses

temporary relief of occasional headaches and minor aches and pains with accompanying sleeplessness

Warnings

Liver warning

This product contains acetaminophen. Severe liver damage may occur if you take

- more than 4,000 mg of acetaminophen in 24 hours
- with other drugs containing acetaminophen
- 3 or more alcoholic drinks every day while using this product

Allergy alert

acetaminophen may cause severe skin reactions. Symptoms may include:

- skin reddening
- blisters
- rash

If a skin reaction occurs, stop use and seek medical help right away.

Do not use

- with any other drug containing acetaminophen (prescription or nonprescription). If you are not sure whether a drug contains acetaminophen, ask a doctor or pharmacist.
- with any other product containing diphenhydramine, even one used on skin
- in children under 12 years of age
- if you have ever had an allergic reaction to this product or any of its ingredients

Ask a doctor before use if you have

- liver disease
- a breathing problem such as emphysema or chronic bronchitis
- trouble urinating due to an enlarged prostate gland
- glaucoma

Ask a doctor or pharmacist before use if you are

- taking the blood thinning drug warfarin
- taking sedatives or tranquilizers

When using this product

- drowsiness will occur
- avoid alcoholic drinks
- do not drive a motor vehicle or operate machinery

Stop use and ask a doctor if

- sleeplessness persists continuously for more than 2 weeks. Insomnia may be a symptom of serious underlying medical illness.
- pain gets worse or lasts more than 10 days
- fever gets worse or lasts more than 3 days
- redness or swelling is present
- new symptoms occur

These could be signs of a serious condition.

PREGNANCY OR BREAST FEEDING

If pregnant or breast-feeding,ask a health professional before use.

Keep out of reach of children.

Overdose warning

In case of overdose, get medical help or contact a Poison Control Center right away (1-800-222-1222). Quick medical attention is critical for adults as well as for children even if you do not notice any signs or symptoms.

Directions

- do not take more than directed (see overdose warning)

adults and children 12 years and over | - take 2 caplets at bedtime - do not take more than 2 caplets of this product in 24 hours
children under 12 years | - do not use

Other information

- store between 20-25°C (68-77°F) in a dry place
- retain carton for complete product information

Inactive ingredients

colloidal silicon dioxide, copovidone, croscarmellose sodium, FD&C blue #1, hypromellose, lactose, magnesium stearate, microcrystalline cellulose, polyethylene glycol, povidone, pregelatinized starch, sodium starch glycolate, stearic acid, titanium dioxide

Questions?

1-844-705-4384

PRINCIPAL DISPLAY PANEL

NDC 85828-095-03

Compare to active ingredients in Tylenol® PM Extra Strength Caplets*

EXTRA STRENGTH

Acetaminophen PM

ACETAMINOPHEN, 500 mg

Diphenhydramine HCl, 25 mg

Pain Reliever / Nighttime Sleep Aid

For Adults

GO

Actual Size

100 CAPLETS